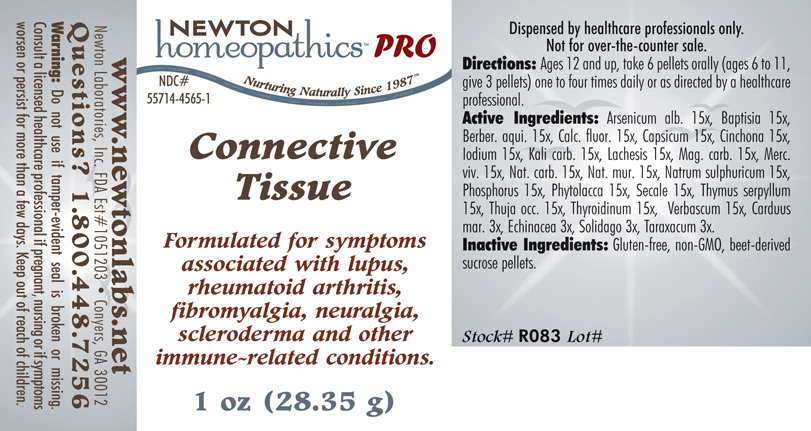 DRUG LABEL: Connective Tissue 
NDC: 55714-4565 | Form: PELLET
Manufacturer: Newton Laboratories, Inc.
Category: homeopathic | Type: HUMAN PRESCRIPTION DRUG LABEL
Date: 20110601

ACTIVE INGREDIENTS: Arsenic Trioxide 15 [hp_X]/1 g; Baptisia Tinctoria 15 [hp_X]/1 g; Mahonia Aquifolium Root Bark 15 [hp_X]/1 g; Calcium Fluoride 15 [hp_X]/1 g; Capsicum 15 [hp_X]/1 g; Iodine 15 [hp_X]/1 g; Potassium Carbonate 15 [hp_X]/1 g; Lachesis Muta Venom 15 [hp_X]/1 g; Magnesium Carbonate 15 [hp_X]/1 g; Mercury 15 [hp_X]/1 g; Sodium Carbonate 15 [hp_X]/1 g; Sodium Chloride 15 [hp_X]/1 g; Sodium Sulfate 15 [hp_X]/1 g; Phosphorus 15 [hp_X]/1 g; Phytolacca Americana Root 15 [hp_X]/1 g; Claviceps Purpurea Sclerotium 15 [hp_X]/1 g; Thuja Occidentalis Leafy Twig 15 [hp_X]/1 g; Thymus Serpyllum 15 [hp_X]/1 g; Thyroid, Unspecified 15 [hp_X]/1 g; Verbascum Thapsus 15 [hp_X]/1 g; Silybum Marianum Seed 3 [hp_X]/1 g; Echinacea, Unspecified 3 [hp_X]/1 g; Solidago Virgaurea Flowering Top 3 [hp_X]/1 g; Taraxacum Officinale 3 [hp_X]/1 g; Cinchona Bark 15 [hp_X]/1 g
INACTIVE INGREDIENTS: Sucrose

Connective Tissue

INDICATIONS & USAGE SECTION

Connective Tissue Formulated for symptoms associated with lupus, rheumatoid arthritis, fibromyalgia, neuralgia, scleroderma and other immune-related conditions.

DOSAGE & ADMINISTRATION SECTION

Directions: Ages 12 and up, take 6 pellets orally (ages 6 to 11, give 3 pellets) one to four times daily or as directed by a healthcare professional.

ACTIVE INGREDIENT SECTION

Arsenicum alb. 15x, Baptisia 15x, Berber. aqui. 15x, Calc. fluor. 15x, Capsicum 15x, Cinchona 15x, Iodium 15x, Kali carb. 15x, Lachesis 15x, Mag. carb. 15x, Merc. viv. 15x, Nat. carb. 15x, Nat. mur. 15x, Natrum sulphuricum 15x, Phosphorus 15x, Phytolacca 15x, Secale 15x, Thymus serpyllum15x, Thuja occ. 15x, Thyroidinum 15x, Verbascum 15x, Carduus mar. 3x, Echinacea 3x, Solidago 3x, Taraxacum 3x.

INACTIVE INGREDIENT SECTION

Inactive Ingredients: Gluten-free, non-GMO, beet-derived sucrose pellets.

PURPOSE SECTION

Formulated for symptoms associated with lupus, rheumatoid arthritis, fibromyalgia, neuralgia, scleroderma and other immune-related conditions.

QUESTIONS? SECTION

www.newtonlabs.net Newton Laboratories, Inc. FDA Est # 1051203 - Conyers, GA 30012
Questions? 1.800.448.7256

WARNINGS SECTION

Warning: Do not use if tamper - evident seal is broken or missing. Consult a licensed healthcare professional if pregnant, nursing or if symptoms worsen or persist for more than a few days. Keep out of reach of children.

PREGNANCY OR BREAST FEEDING SECTION

Consult a licensed healthcare professional if pregnant, nursing or if symptoms worsen or persist for more than a few days.

KEEP OUT OF REACH OF CHILDREN SECTION

Keep out of reach of children.